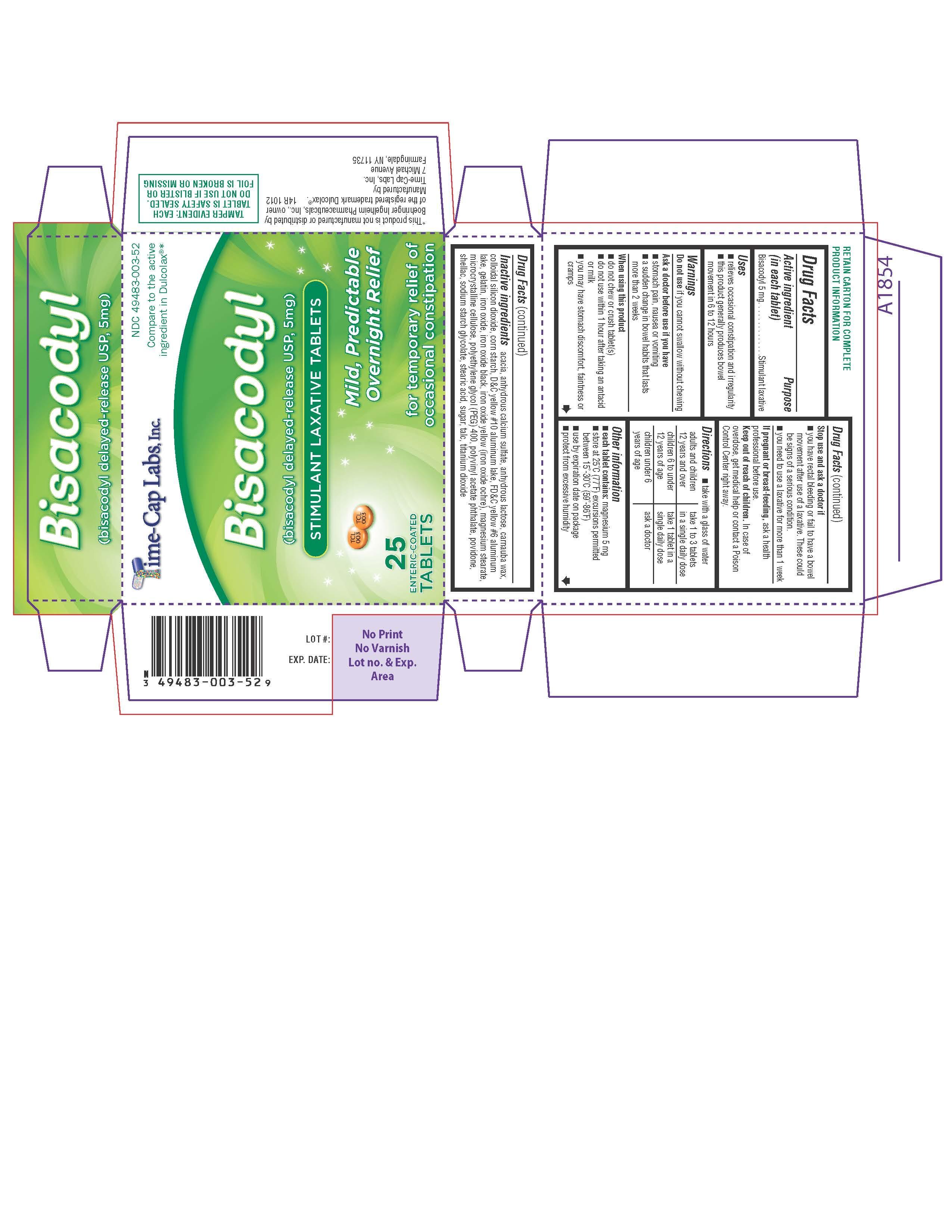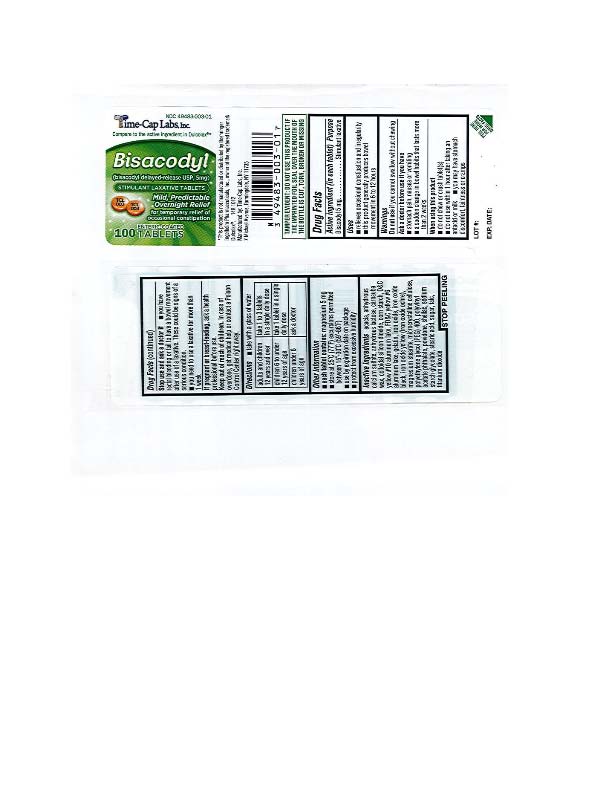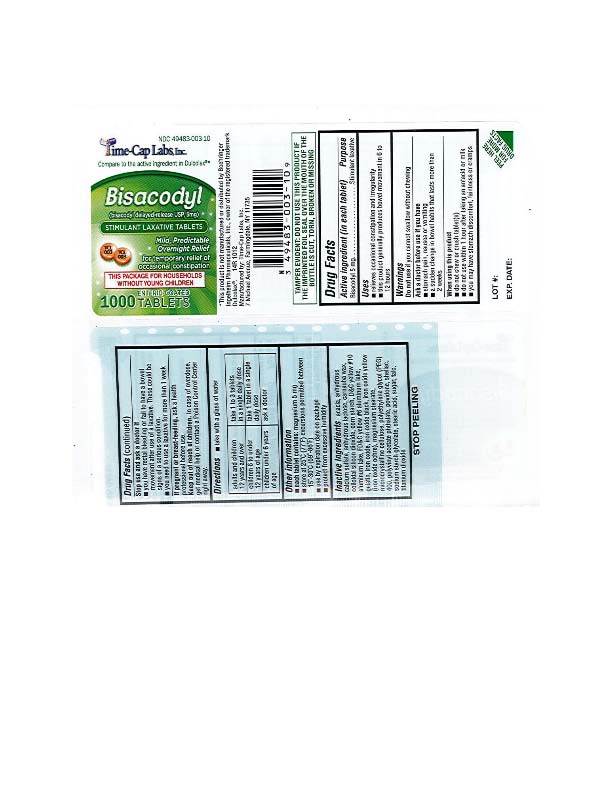 DRUG LABEL: STIMULANT LAXATIVE
NDC: 49483-003 | Form: TABLET, DELAYED RELEASE
Manufacturer: TIME CAP LABORATORIES, INC.
Category: otc | Type: HUMAN OTC DRUG LABEL
Date: 20190927

ACTIVE INGREDIENTS: BISACODYL 5 mg/1 1
INACTIVE INGREDIENTS: ACACIA; CALCIUM SULFATE ANHYDROUS; ANHYDROUS LACTOSE; CARNAUBA WAX; SILICON DIOXIDE; STARCH, CORN; D&C YELLOW NO. 10; FD&C YELLOW NO. 6; GELATIN; FERROSOFERRIC OXIDE; FERRIC OXIDE YELLOW; MAGNESIUM STEARATE; CELLULOSE, MICROCRYSTALLINE; POLYETHYLENE GLYCOL 400; POLYVINYL ACETATE PHTHALATE; POVIDONE; SHELLAC; SODIUM STARCH GLYCOLATE TYPE A CORN; STEARIC ACID; SUCROSE; TALC; TITANIUM DIOXIDE

14R - BISACODAYL-TCL

ACTIVE INGREDIENT

In each tablet: Bisacodyl 5mg

INACTIVE INGREDIENT

Acadia, Anhydrous Calcium Sulfate, Anhydrous Lactose, Carnauba Wax, Colloidal Silicon Dioxide, Corn Starch, D&C Yellow #10 Aluminum Lake, FD&C yellow #6 aluminum lake, Gelatin, Iron Oxide, Iron Oxide Black, Iron Oxide Yellow(Iron Oxide Ochre), Magnesium Stearate, Microcrystalline Cellulose, Polyethylene Glycol (PEG) 400, Polyvinyl Acetate Phthalates, Povidone, Shellac, Sodium Starch Glycolate, Stearic Acid, Sugar, Talc, Titanium Dioxide

PURPOSE

Stimulant Laxative

Keep out of Reach of Children: In case of overdose, get medical help or contact a Poison Control Center right away.

Uses:

- relieves occasional constipation and irregularity
- this product generally produces a bowel movement in 6 to 12 hours

WARNINGS

Warning: Do not use if you cannot swallow without chewing.

Ask a doctor before use if you have: stomach pain, nausea or vomiting; A sudden change in bowel habits that lasts more than two weeks.

When using this product: Do not chew or crush tablet(s); Do not use within 1 hour after taking an antacid or milk; Do not use this product if you have stomach discomfort, faintness or cramps.

DOSAGE AND ADMINISTRATION

- adults and children 12 years and over: take 1 to 3 tablets in a single daily dose
- children 6 to under 12 years: take 1 tablet in a single daily dose
- children under 6 years: ask a doctor